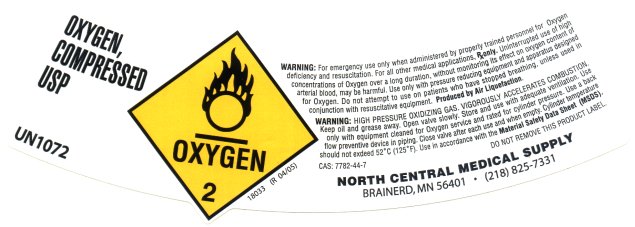 DRUG LABEL: oxygen
NDC: 45028-001 | Form: GAS
Manufacturer: North Central Medical Supply, Inc.
Category: prescription | Type: HUMAN PRESCRIPTION DRUG LABEL
Date: 20181114

ACTIVE INGREDIENTS: OXYGEN 992 mL/1 L

oxygen, compressed

OXYGEN, COMPRESSED USP
UN1072
WARNING: For emergency use only when administered by properly trained personnel for Oxygen deficiency and resuscitation. For all other medical applications, RX only. Uninterrupted use of high concentrations of Oxygen over a long duration, without monitoring its effect on oxygen content of arterial blood, may be harmful. Use only with pressure reducing equipment and apparatus designed for Oxygen. Do not attempt to use on patients who have stopped breathing, unless used in conjunction with resuscitative equipment. Produced by Air Liquefaction.

WARNING: HIGH PRESSURE OXIDIZING GAS. VIGOROUSLY ACCELERATES COMBUSTION. Keep oil and grease away. Open valve slowly. Store and use with adequate ventilation. Use only with equipment cleaned for Oxygen service and rated for cylinder pressure. Use a back flow preventive device in piping. Close valve after each use and when empty. Cylinder temperature should not exceed 52◦C (125◦F). Use in accordance with the Material Safety Data Sheet (MSDS).
CAS: 7782-44-7
DO NOT REMOVE THIS PRODUCT LABEL
18033 (R 04/05)
NORTH CENTRAL MEDICAL SUPPLY
BRAINERD, MN 56401 . (218) 825-7331